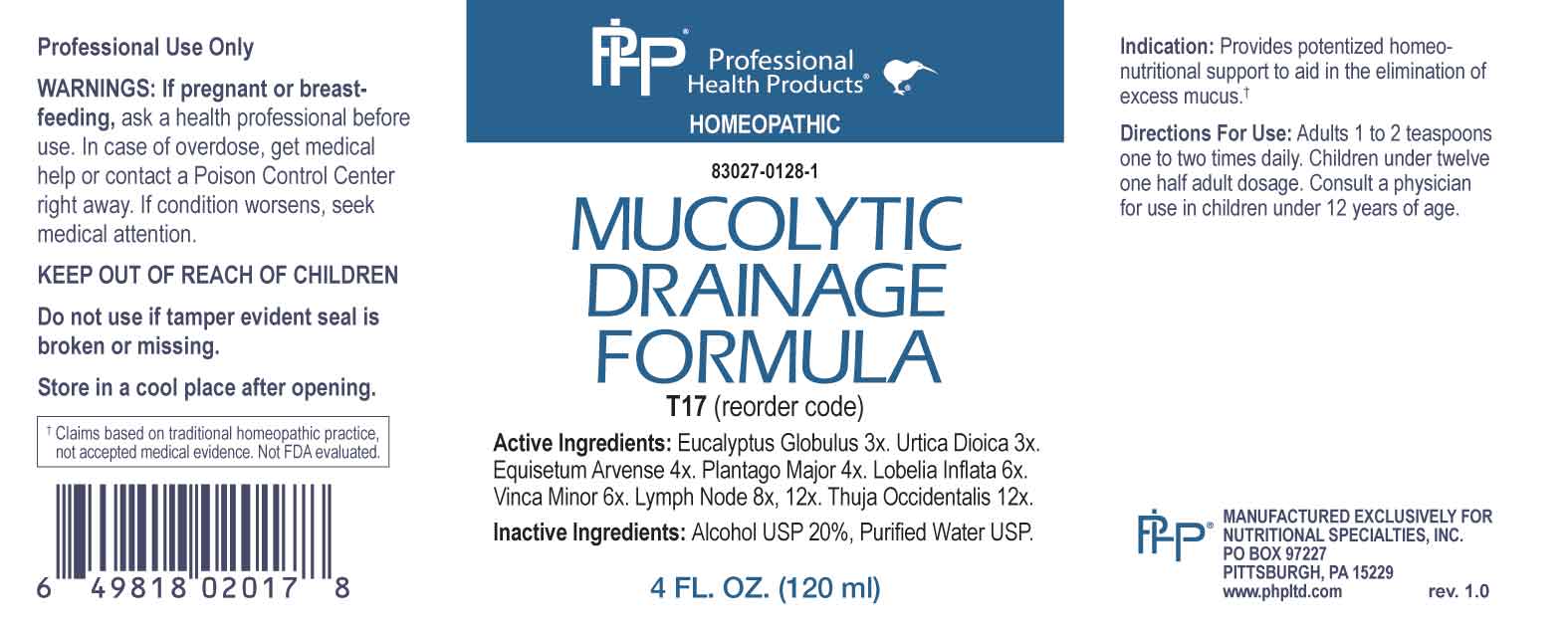 DRUG LABEL: Mucolytic Drainage Formula
NDC: 83027-0128 | Form: LIQUID
Manufacturer: Nutritional Specialties, Inc.
Category: homeopathic | Type: HUMAN OTC DRUG LABEL
Date: 20240430

ACTIVE INGREDIENTS: EUCALYPTUS GLOBULUS LEAF 3 [hp_X]/1 mL; URTICA DIOICA WHOLE 3 [hp_X]/1 mL; EQUISETUM ARVENSE TOP 4 [hp_X]/1 mL; PLANTAGO MAJOR WHOLE 4 [hp_X]/1 mL; LOBELIA INFLATA WHOLE 6 [hp_X]/1 mL; PERVINCA MINOR WHOLE 6 [hp_X]/1 mL; SUS SCROFA LYMPH 8 [hp_X]/1 mL; THUJA OCCIDENTALIS LEAFY TWIG 12 [hp_X]/1 mL
INACTIVE INGREDIENTS: WATER; ALCOHOL

DRUG FACTS:

ACTIVE INGREDIENTS:

Eucalyptus Globulus 3X, Urtica Dioica 3X, Equisetum Arvense 4X, Plantago Major 4X, Lobelia Inflata 6X, Vinca Minor 6X, Lymph Node (Suis) 8X, 12X, Thuja Occidentalis 12X.

PURPOSE:

Provides potentized homeo-nutritional support to aid in the elimination of excess mucus.†

†Claims based on traditional homeopathic practice, not accepted medical evidence. Not FDA evaluated.

WARNINGS:

Professional Use Only

If pregnant or breast-feeding, ask a health professional before use.

In case of overdose, get medical help or contact a Poison Control Center right away.

If condition worsens, seek medical attention.

KEEP OUT OF REACH OF CHILDREN

Do not use if tamper evident seal is broken or missing.

Store in a cool place after opening

KEEP OUT OF REACH OF CHILDREN:

In case of overdose, get medical help or contact a Poison Control Center right away.

DIRECTIONS:

Adults: 1 to 2 teaspoons one to two times daily. Children under twelve one half adult dosage. Consult a physician for use in children under 12 years of age.

INDICATIONS:

Provides potentized homeo-nutritional support to aid in the elimination of excess mucus.†

†Claims based on traditional homeopathic practice, not accepted medical evidence. Not FDA evaluated.

INACTIVE INGREDIENTS:

Alcohol USP 20%, Purified Water USP.

QUESTIONS:

MANUFACTURED EXCLUSIVELY FOR

NUTRITIONAL SPECIALTIES, INC.

PO BOX 97227

PITTSBURG, PA 15229

www.phpltd.com

PACKAGE LABEL DISPLAY:

Professional

Health Products

HOMEOPATHIC

NDC 83027-0128-1

MUCOLYTIC DRAINAGE

FORMULA

4 FL. OZ (120 ml)